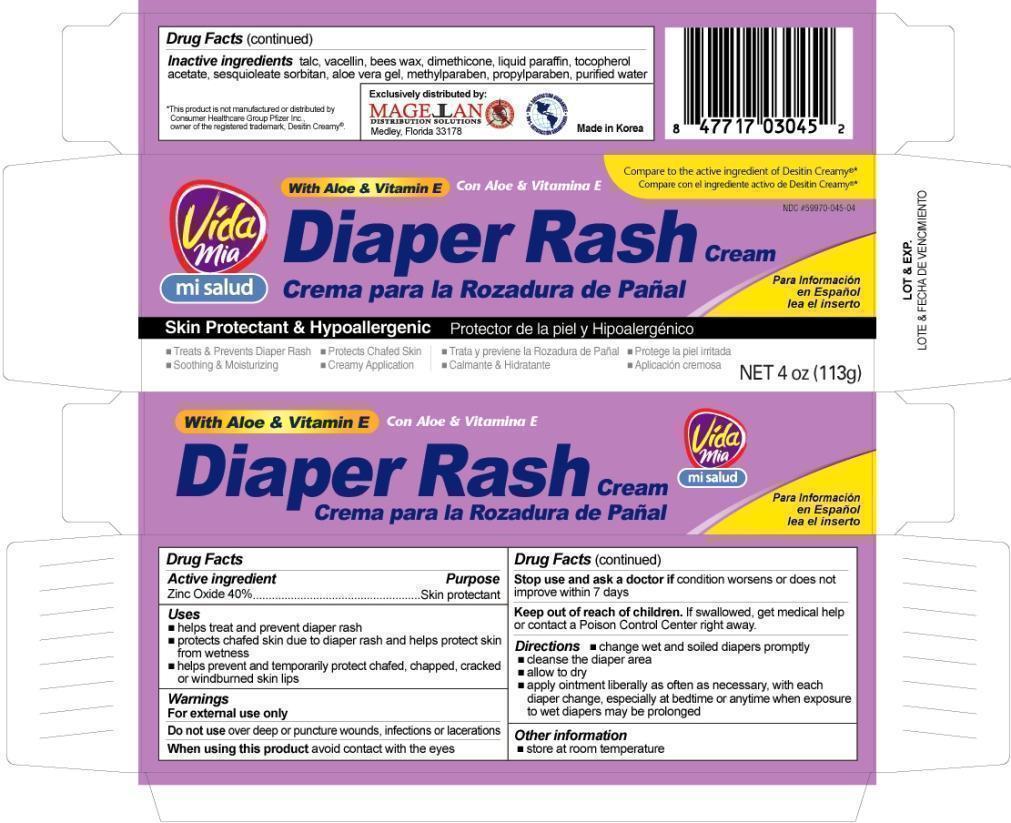 DRUG LABEL: Diaper Rash
NDC: 59970-045 | Form: CREAM
Manufacturer: Navarro Discount Pharmacies,LLC
Category: otc | Type: HUMAN OTC DRUG LABEL
Date: 20120713

ACTIVE INGREDIENTS: ZINC OXIDE 0.40 g/1 g
INACTIVE INGREDIENTS: TALC; APIS MELLIFERA; MINERAL OIL; TOCOPHEROL; SORBITAN SESQUIOLEATE; ALOE VERA LEAF; METHYLPARABEN; PROPYLPARABEN; WATER

Drug Facts

Active ingredient

Zinc Oxide 40%

Purpose

Skin Protectant

Uses

- helps treat and prevent diaper rash
- protects chafed skin due to diaper rash and helps protect skin from wetness
- helps prevent and temporarily protect chafed, chapped, cracked or windburned skin lips

Warnings

For external use only

Do not use

over deep or puncture wounds, infections or lacerations

When using this product

avoid contact with the eyes

Stop use and ask a doctor

if condition worsens or does not improve within 7 days.

Keep out of reach of children.

If swallowed, get medical help or contact a Poison Control Center right away.

Directions

- cleanse the diaper area
- allow to dry
- apply ointment liberally as often as necessary, with each diaper change, especially at bedtime or anytime when exposure to wet diapers may be prolonged

Other information

- store at room temperature

Inactive ingredients

Talc, Vacellin, Bees wax, Dimethicone, Liquid paraffin, Tocopherol acetate, Sesquioleate sorbitan, Aloe vera gel, Methylparaben, Propylparaben, Purified water

Package label

Vida Mia Diaper Rash Cream